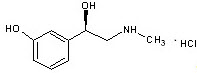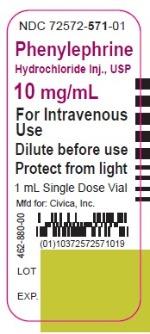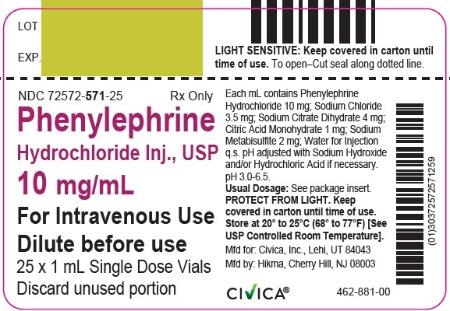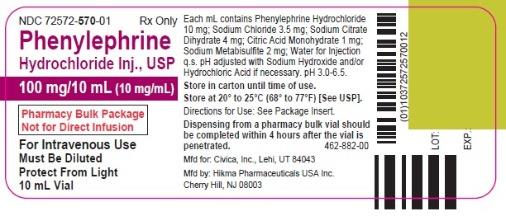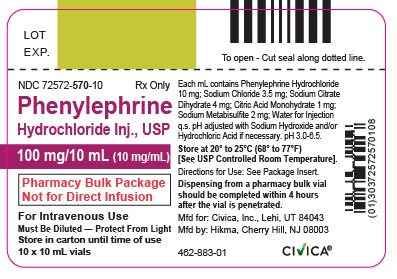 DRUG LABEL: Phenylephrine Hydrochloride
NDC: 72572-570 | Form: INJECTION
Manufacturer: Civica, Inc.
Category: prescription | Type: HUMAN PRESCRIPTION DRUG LABEL
Date: 20241226

ACTIVE INGREDIENTS: PHENYLEPHRINE HYDROCHLORIDE 10 mg/1 mL
INACTIVE INGREDIENTS: SODIUM CHLORIDE 3.5 mg/1 mL; TRISODIUM CITRATE DIHYDRATE 4  mg/1 mL; CITRIC ACID MONOHYDRATE 1  mg/1 mL; SODIUM METABISULFITE 2 mg/1 mL; WATER; SODIUM HYDROXIDE; HYDROCHLORIC ACID

HIGHLIGHTS OF PRESCRIBING INFORMATION

These highlights do not include all the information needed to use PHENYLEPHRINE HYDROCHLORIDE safely and effectively. See full prescribing information for PHENYLEPHRINE HYDROCHLORIDE.
PHENYLEPHRINE HYDROCHLORIDE injection, for intravenous use
Initial U.S. Approval: 2012

RECENT MAJOR CHANGES

Dosage and Administration, Pharmacy Bulk Vials (2.6) 6/2019

1 INDICATIONS AND USAGE

Phenylephrine Hydrochloride is an alpha-1 adrenergic receptor agonist indicated for increasing blood pressure in adults with clinically important hypotension resulting primarily from vasodilation, in such settings as septic shock or anesthesia.

2 DOSAGE AND ADMINISTRATION

Dilute before administration. (2.1)
Dosing for Perioperative Hypotension
• Intravenous bolus administration: 50 mcg to 250 mcg (2.4)
• Intravenous continuous infusion: 0.5 mcg/kg/minute to 1.4 mcg/kg/minute titrated to effect (2.4)
Dosing for Patients with Vasodilatory Shock
• Intravenous continuous infusion: 0.5 mcg/kg/minute to 6 mcg/kg/minute titrated to effect (2.5)

3 DOSAGE FORMS AND STRENGTHS

Injection: 10 mg/mL supplied as a:

1 mL single dose vial (3, 11, 16)

10 mL pharmacy bulk package vial (3, 11, 16)

4 CONTRAINDICATIONS

- Hypersensitivity to it or any of its components (4)

5 WARNINGS AND PRECAUTIONS

- Severe bradycardia and decreased cardiac output: (5.2)
- Extravasation: during intravenous administration may cause necrosis or sloughing of tissue (5.4)
- Concomitant use with oxytocic drugs: pressor effect of sympathomimetic pressor amines is potentiated (5.5)
- Allergic-type reactions: Sulfite (5.6)

6 ADVERSE REACTIONS

Most common adverse reactions: nausea and vomiting, headache, nervousness (6)

To report SUSPECTED ADVERSE REACTIONS, contact Hikma Pharmaceuticals USA Inc. at 1-877-845-0689 or FDA at 1-800-FDA-1088 or www.fda.gov/medwatch.

7 DRUG INTERACTIONS

- Agonistic effects with monoamine oxidase inhibitors (MAOI), β-adrenergic blocking agents, α-2 adrenergic agonists, steroids, tricyclic antidepressants, norepinephrine transport inhibitors, ergot alkaloids, centrally-acting sympatholytic agents and atropine sulfate (7.1)
- Antagonistic effects on and by α-adrenergic blocking agents (7.2)

FULL PRESCRIBING INFORMATION

1 INDICATIONS AND USAGE

Phenylephrine Hydrochloride is an alpha-1 adrenergic receptor agonist indicated for increasing blood pressure in adults with clinically important hypotension resulting primarily from vasodilation, in such settings as septic shock or anesthesia.

2 DOSAGE AND ADMINISTRATION

2.1 General Administration Instructions

Phenylephrine hydrochloride must be diluted before administration as bolus intravenous infusion or continuous intravenous infusion.

Inspect the solution for particulate matter and discoloration prior to administration. The diluted solution should not be held for more than 4 hours at room temperature or for more than 24 hours under refrigerated conditions. Discard any unused portion.

During phenylephrine hydrochloride administration:

- Correct intravascular volume depletion.
- Correct acidosis. Acidosis may reduce the effectiveness of phenylephrine.

2.2 Preparing a 100 mcg/mL Solution for Bolus Intravenous Administration

For bolus intravenous administration, withdraw 10 mg (1 mL of a 10 mg/mL concentration) of phenylephrine hydrochloride injection and dilute with 99 mL of 5% Dextrose Injection, USP or 0.9% Sodium Chloride Injection, USP. This will yield a final concentration of 100 mcg/mL. Withdraw an appropriate dose from the 100 mcg/mL solution prior to bolus intravenous administration.

2.3 Preparing a Solution for Continuous Intravenous Infusion

For continuous intravenous infusion, withdraw 10 mg (1 mL of 10 mg/mL concentration) of phenylephrine hydrochloride injection and add to 500 mL of 5% Dextrose Injection, USP or 0.9% Sodium Chloride Injection, USP (providing a final concentration of 20 mcg/mL).

2.4 Dosing for Perioperative Setting

In adult patients undergoing surgical procedures with either neuraxial anesthesia or general anesthesia:

- 50 mcg to 250 mcg by intravenous bolus administration. The most frequently reported initial bolus dose is 50 mcg or 100 mcg.
- 0.5 mcg/kg/min to 1.4 mcg/kg/min by intravenous continuous infusion, titrated to blood pressure goal.

2.5 Dosing for Septic or Other Vasodilatory Shock

In adult patients with septic or other vasodilatory shock:

- No bolus.
- 0.5 mcg/kg/min to 6 mcg/kg/min by intravenous continuous infusion, titrated to blood pressure goal. Doses above 6 mcg/kg/min do not show significant incremental increase in blood pressure.

2.6 Directions for Dispensing from Pharmacy Bulk Vial

The Pharmacy Bulk Vial is intended for dispensing of single doses to multiple patients in a pharmacy admixture program and is restricted to the preparation of admixtures for infusion. Each closure shall be penetrated only one time with a suitable sterile transfer device or dispensing set that allows measured dispensing of the contents. The Pharmacy Bulk Vial is to be used only in a suitable work area such as a laminar flow hood (or an equivalent clean air compounding area). Dispensing from a pharmacy bulk vial should be completed within 4 hours after the vial is penetrated.

3 DOSAGE FORMS AND STRENGTHS

Injection: 10 mg/mL phenylephrine hydrochloride is supplied in two vial sizes:

1 mL single dose vial (10 mg of phenylephrine hydrochloride per vial)

10 mL Pharmacy Bulk Package vial (100 mg of phenylephrine hydrochloride per vial) that will provide ten 1 mL single doses

4 CONTRAINDICATIONS

The use of phenylephrine hydrochloride is contraindicated in patients with:

- Hypersensitivity to it or any of its components

5 WARNINGS AND PRECAUTIONS

5.1 Exacerbation of Angina, Heart Failure, or Pulmonary Arterial Hypertension

Because of its pressor effects, phenylephrine hydrochloride can precipitate angina in patients with severe arteriosclerosis or history of angina, exacerbate underlying heart failure, and increase pulmonary arterial pressure.

5.2 Bradycardia

Phenylephrine hydrochloride can cause severe bradycardia and decreased cardiac output.

5.3 Risk in Patients with Autonomic Dysfunction

The pressor response to adrenergic drugs, including phenylephrine, can be increased in patients with autonomic dysfunction, as may occur with spinal cord injuries.

5.4 Skin and Subcutaneous Necrosis

Extravasation of phenylephrine can cause necrosis or sloughing of tissue.

5.5 Pressor Effect with Concomitant Oxytocic Drugs

Oxytocic drugs potentiate the pressor effect of sympathomimetic pressor amines including phenylephrine hydrochloride [see Drug Interactions (7.1)], with the potential for hemorrhagic stroke.

5.6 Allergic Reactions

This product contains sodium metabisulfite, a sulfite that may cause allergic-type reactions, including anaphylactic symptoms and life-threatening or less severe asthmatic episodes in certain susceptible people. The overall prevalence of sulfite sensitivity in the general population is unknown and probably low. Sulfite sensitivity is seen more frequently in asthmatic than in nonasthmatic people.

5.7 Peripheral and Visceral Ischemia

Phenylephrine hydrochloride can cause excessive peripheral and visceral vasoconstriction and ischemia to vital organs, particularly in patients with extensive peripheral vascular disease.

5.8 Renal Toxicity

Phenylephrine hydrochloride can increase the need for renal replacement therapy in patients with septic shock. Monitor renal function.

6 ADVERSE REACTIONS

The following adverse reactions associated with the use of phenylephrine hydrochloride were identified in the literature. Because these reactions are reported voluntarily from a population of uncertain size, it is not always possible to estimate their frequency reliably or to establish a causal relationship to drug exposure.

Cardiac disorders: Bradycardia, AV block, ventricular extrasystoles, myocardial ischemia

Gastrointestinal disorders: Nausea, vomiting

General disorders and administrative site conditions: Chest pain, extravasation

Immune system disorders: Sulfite sensitivity

Nervous system disorders: Headache, nervousness, paresthesia, tremor

Psychiatric disorders: Excitability

Respiratory: Pulmonary edema, rales

Skin and subcutaneous tissue disorders: Diaphoresis, pallor, piloerection, skin blanching, skin necrosis with extravasation

Vascular disorders: Hypertensive crisis

7 DRUG INTERACTIONS

7.1 Agonists

The pressor effect of phenylephrine hydrochloride is increased in patients receiving:

- Monoamine oxidase inhibitors (MAOI), such as selegiline.
- β-adrenergic blockers
- α-2 adrenergic agonists, such as clonidine
- Steroids
- Tricyclic antidepressants
- Norepinephrine transport inhibitors, such as atomoxetine
- Ergot alkaloids, such as methylergonovine maleate
- Centrally-acting sympatholytic agents, such as guanfacine or reserpine
- Atropine sulfate

7.2 Antagonists

α-adrenergic blocking agents, including phenothiazines (e.g., chlorpromazine) and amiodarone block phenylephrine and are in turn blocked by phenylephrine.

8 USE IN SPECIFIC POPULATIONS

8.1 Pregnancy

Pregnancy Category C

Animal reproduction studies have not been conducted with intravenous phenylephrine. It is also not known whether phenylephrine can cause fetal harm when administered to a pregnant woman or can affect reproduction capacity. Phenylephrine hydrochloride should be given to a pregnant woman only if clearly needed.

8.2 Labor and Delivery

The most common maternal adverse reactions reported in studies of phenylephrine use during neuraxial anesthesia during cesarean delivery include nausea and vomiting, which are commonly associated with hypotension, bradycardia, reactive hypertension, and transient arrhythmias. Phenylephrine does not appear to cause a decrease in placental perfusion sufficient to alter either the neonate Apgar scores or blood-gas status.

8.3 Nursing Mothers

It is not known whether this drug is excreted in human milk.

8.4 Pediatric Use

Safety and effectiveness in pediatric patients have not been established.

8.5 Geriatric Use

Clinical studies of phenylephrine did not include sufficient numbers of subjects aged 65 and over to determine whether they respond differently from younger subjects. Other reported clinical experience has not identified differences in responses between the elderly and younger patients. In general, dose selection for an elderly patient should be cautious, usually starting at the low end of the dosing range, reflecting the greater frequency of decreased hepatic, renal, or cardiac function, and of concomitant disease or other drug therapy.

8.6 Hepatic Impairment

In patients with liver cirrhosis [Child Pugh Class A (n=3), Class B (n=5) and Class C (n=1)], dose-response data indicate decreased responsiveness to phenylephrine. Consider using larger doses than usual in hepatic impaired subjects.

8.7 Renal Impairment

In patients with end stage renal disease (ESRD) undergoing hemodialysis, dose-response data indicates increased responsiveness to phenylephrine. Consider using lower doses of phenylephrine hydrochloride in ESRD patients.

10 OVERDOSAGE

Overdose of phenylephrine hydrochloride can cause a rapid rise in blood pressure. Symptoms of overdose include headache, vomiting, hypertension, reflex bradycardia, and cardiac arrhythmias including ventricular extrasystoles and ventricular tachycardia, and may cause a sensation of fullness in the head and tingling of the extremities.

Consider using an α-adrenergic antagonist.

11 DESCRIPTION

Phenylephrine hydrochloride is a synthetic sympathomimetic agent in sterile form for parenteral injection. Chemically, phenylephrine hydrochloride is (-)-m-Hydroxy-α-[(methylamino)methyl]benzyl alcohol hydrochloride and has the following structural formula:

Phenylephrine hydrochloride is very soluble in water, freely soluble in ethanol, and insoluble in chloroform and ethyl ether. Phenylephrine hydrochloride is sensitive to light.

Phenylephrine Hydrochloride Injection, USP is a clear, colorless, aqueous solution that is essentially free of visible foreign matter. Each mL contains: Phenylephrine Hydrochloride 10 mg; Sodium Chloride 3.5 mg; Sodium Citrate Dihydrate 4 mg; Citric Acid Monohydrate 1 mg; and Sodium Metabisulfite 2 mg in Water for Injection. The pH may be adjusted in the range of 3.0 to 6.5 with Sodium Hydroxide and/or Hydrochloric Acid, if necessary.

12 CLINICAL PHARMACOLOGY

12.1 Mechanism of Action

Phenylephrine hydrochloride is an α-1 adrenergic receptor agonist.

12.2 Pharmacodynamics

Phenylephrine is the active moiety. Metabolites are inactive at both the α-1and α-2 adrenergic receptors. Following parenteral administration of phenylephrine hydrochloride, increases in systolic blood pressure, diastolic blood pressure, mean arterial blood pressure, and total peripheral vascular resistance are observed. The onset of blood pressure increase following an intravenous bolus phenylephrine hydrochloride administration is rapid and the effect may persist for up to 20 minutes. As mean arterial pressure increases following parenteral doses, vagal activity also increases, resulting in reflex bradycardia.

Most vascular beds are constricted, including renal, splanchnic, and hepatic.

12.3 Pharmacokinetics

Following an intravenous infusion of phenylephrine hydrochloride, the effective half-life was approximately 5 minutes. The steady-state volume of distribution (340 L) exceeded the body volume by a factor of 5, suggesting a high distribution into certain organ compartments. The average total serum clearance (2095 mL/min) was close to one-third of the cardiac output.

A mass balance study showed that phenylephrine is extensively metabolized by the liver with only 12% of the dose excreted unchanged in the urine. Deamination by monoamino oxidase is the primary metabolic pathway resulting in the formation of the major metabolite (m-hydroxymandelic acid) which accounts for 57% of the total administered dose.

14 CLINICAL STUDIES

Increases in systolic and mean blood pressure following administration of phenylephrine were observed in 42 literature-based studies in the perioperative setting, including 26 studies where phenylephrine was used in low-risk (ASA 1 and 2) pregnant women undergoing neuraxial anesthesia during cesarean delivery, 3 studies in non-obstetric surgery under neuraxial anesthesia, and 13 studies in patients undergoing surgery under general anesthesia. Mean arterial blood pressure increases were also observed in two double-blind, active-controlled studies in patients with septic shock.

16 HOW SUPPLIED/STORAGE AND HANDLING

Phenylephrine Hydrochloride Injection, USP, 10 mg/mL, is supplied as follows:

- NDC 72572-571-25: 1 mL single dose vials packaged in cartons containing 25 vials per carton
- NDC 72572-570-10: 10 mL Pharmacy Bulk Package vials packed in cartons containing 10 vials per carton

Store at 20°C to 25°C (68°F to 77°F), excursions permitted to 15°C to 30°C (59°F to 86°F) [See USP Controlled Room Temperature]. Protect from light. Keep covered in carton until time of use. The 1 mL vials are for single use only; the 10 mL vial is a pharmacy bulk package. The diluted solution should not be held for more than 4 hours at room temperature or for more than 24 hours under refrigerated conditions. Discard any unused portion.

17 PATIENT COUNSELING INFORMATION

Inform patients, families, or caregivers that the primary side effect of phenylephrine is hypertension and, rarely, hypertensive crisis. Patients may experience bradycardia (slow heart rate), which in some cases may produce heart block or other cardiac arrhythmias, extra ventricular beats, myocardial ischemia in patients with underlying cardiac disease, and pulmonary edema (fluid in the lungs) or rales. Common, less serious symptoms include the following:

- chest pain
- skin or tissue damage if the drug leaks out of the venous catheter into the surrounding tissue
- headache, nervousness, tremor, numbness/tingling (paresthesias) in hands or feet
- nausea, vomiting
- excitability, dizziness, sweating, flushing

PACKAGE LABEL

Manufactured for:
Civica, Inc., Lehi, Utah 84043

Manufactured by:
Hikma Pharmaceuticals USA Inc.
Cherry Hill, NJ 08003

Revised: July 2020 462-884-00

PRINCIPAL DISPLAY PANEL

NDC 72572-571-01
Phenylephrine
Hydrochloride Inj., USP
10 mg/mL
For Intravenous
Use
Dilute before use
Protect from light
1 mL Single Dose Vial

NDC 72572-571-25 Rx Only
Phenylephrine
Hydrochloride Inj., USP
10 mg/mL
For Intravenous Use
Dilute before use
25 x 1 mL Single Dose Vials
Discard unused portion

PRINCIPAL DISPLAY PANEL

NDC 72572-570-01 Rx Only
Phenylephrine
Hydrochloride Inj., USP
100 mg/10 mL (10 mg/mL)
Pharmacy Bulk Package
Not for Direct Infusion
For Intravenous Use
Must Be Diluted
Protect From Light
10 mL Vial

NDC 72572-570-10 Rx Only
Phenylephrine
Hydrochloride Inj., USP
100 mg/10 mL (10 mg/mL)
Pharmacy Bulk Package
Not for Direct Infusion
For Intravenous Use
Must Be Diluted - Protect From Light
Store in carton until time of use
10 x 10 mL vials